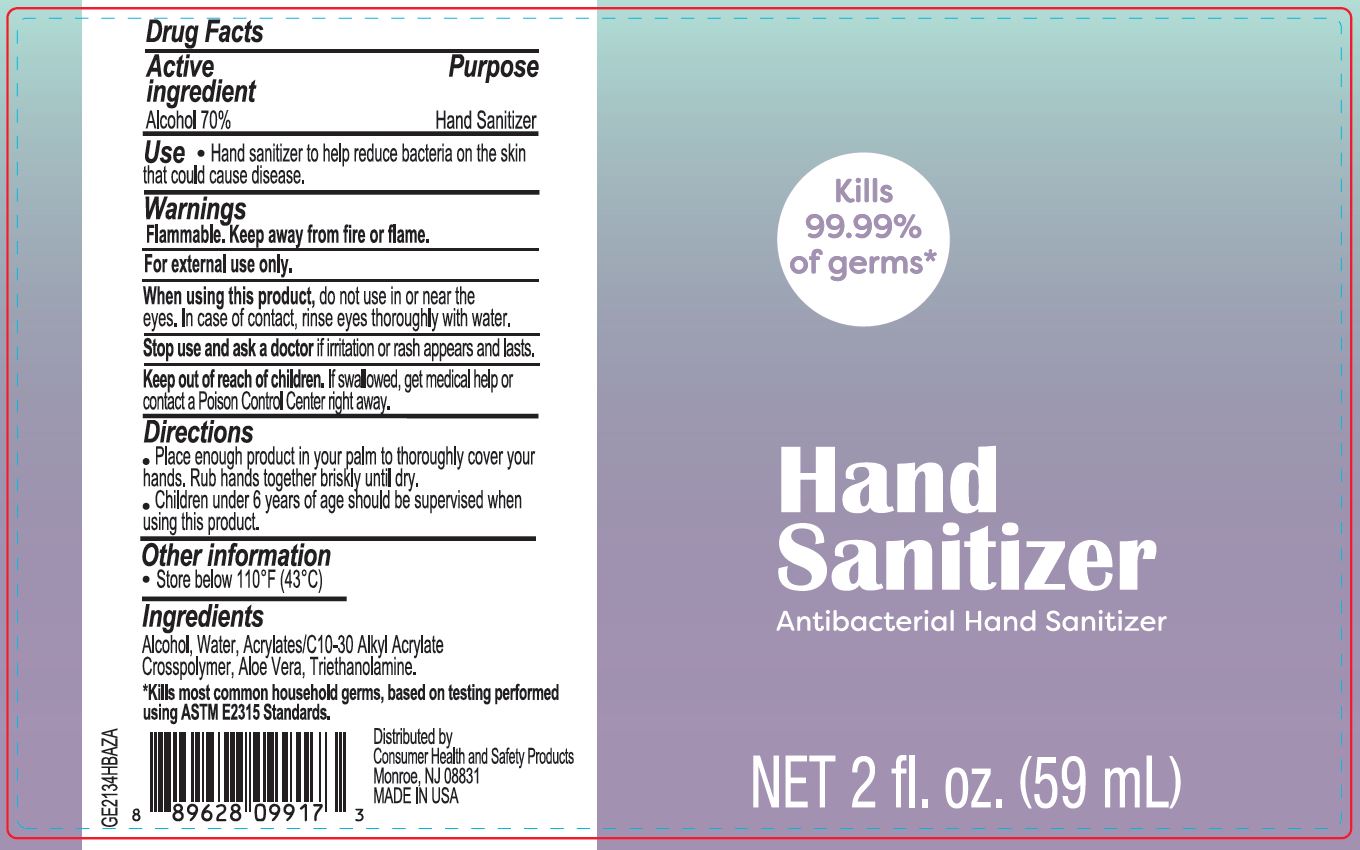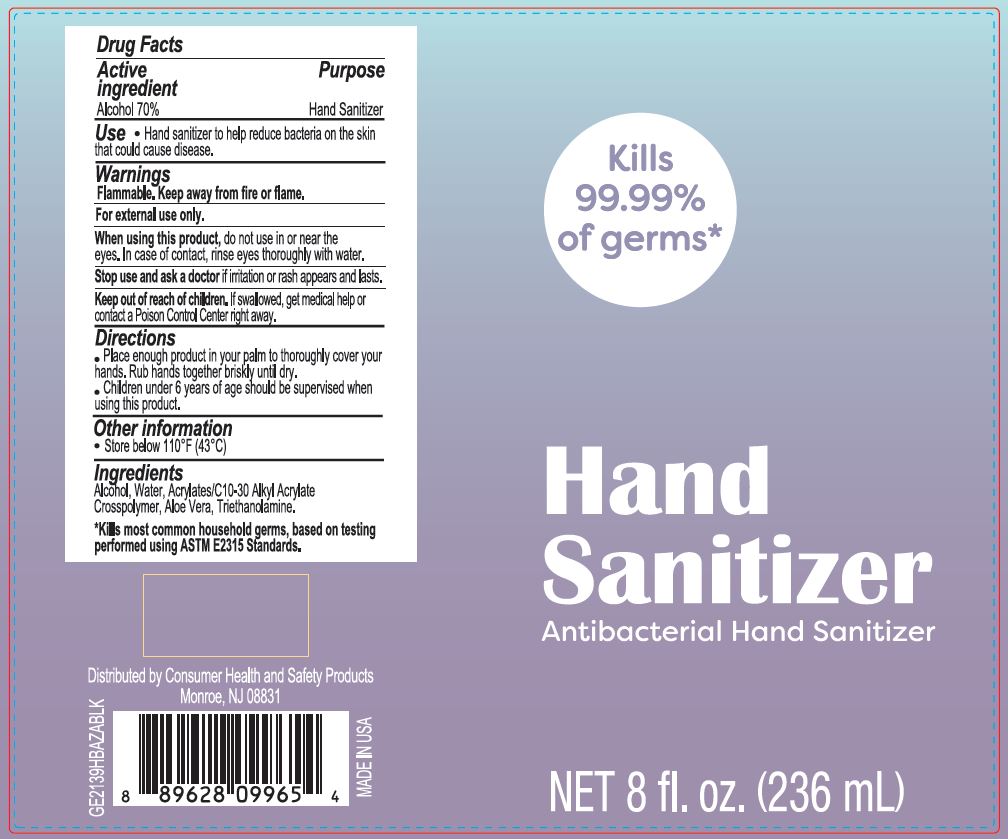 DRUG LABEL: Hand Sanitizer-Antibacterial Hand Sanitizer
NDC: 77968-070 | Form: GEL
Manufacturer: Consumer Health and Safety Products
Category: otc | Type: HUMAN OTC DRUG LABEL
Date: 20200516

ACTIVE INGREDIENTS: ALCOHOL 70 mL/100 mL
INACTIVE INGREDIENTS: POLYACRYLIC ACID (250000 MW) 0.4 mL/100 mL; WATER 29.4 mL/100 mL; ALOE VERA LEAF POLYSACCHARIDES 0.1 mL/100 mL; TROLAMINE 0.1 mL/100 mL

Hand Sanitizer - Antibacterial Hand Sanitizer

Active ingredient

Alcohol 70%

Purpose

Hand Sanitizer

Use

Hand Sanitizer to help reduce bacteria on the skin that could cause disease.

Warnings

Flammable, Keep away from fire or flame.

For External Use only.

When Using this product.

do not use in or near the eyes, in case of contact, rinse throughly with water.

Stop Using this product.

if irritation or rash appears and lasts.

Keep out of Reach of Children

if Swallowed, get medical help or contact a Poison Control Center right away.

Directions

- Place enough product in your palm to throoughly cover your hands. Rub hands together briskly until dry.
- Children under 6 years of age should be supervised when using this product.

Other information

- Store below 110°F (43°C)

Ingredients

Alcohol, Water, Acrylates(C-10/30 Alkyl Acylate) Crosspolymer, Aloe Vera, Triethanolamine.

Package Label - Principal Disaplay Label

60 mL NDC: 77968-070-02

236 mL NDC: 77968-070-01